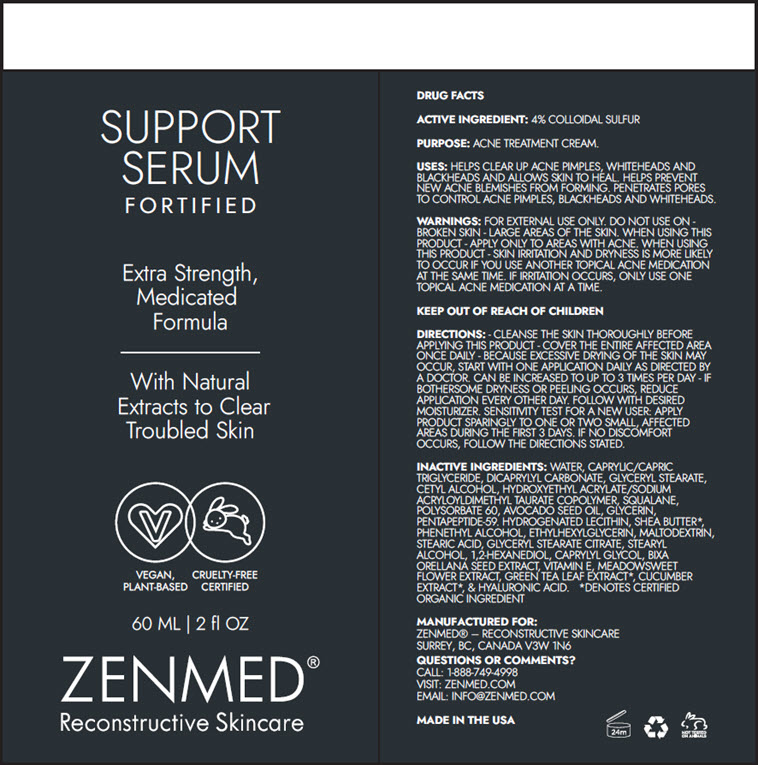 DRUG LABEL: SUPPORT SERUM FORTIFIED
NDC: 83313-0064 | Form: CREAM
Manufacturer: ZENMED Raging Creations Ltd.
Category: otc | Type: HUMAN OTC DRUG LABEL
Date: 20251110

ACTIVE INGREDIENTS: SULFUR 0.04 g/1 mL
INACTIVE INGREDIENTS: WATER; MEDIUM-CHAIN TRIGLYCERIDES; DICAPRYLYL CARBONATE; GLYCERYL MONOSTEARATE; CETYL ALCOHOL; HYDROXYETHYL ACRYLATE/SODIUM ACRYLOYLDIMETHYL TAURATE COPOLYMER (100000 MPA.S AT 1.5%); SQUALANE; POLYSORBATE 60; GLYCERIN; PENTAPEPTIDE-59; SHEA BUTTER; PHENYLETHYL ALCOHOL; ETHYLHEXYLGLYCERIN; MALTODEXTRIN; STEARIC ACID; GLYCERYL STEARATE CITRATE; STEARYL ALCOHOL; 1,2-HEXANEDIOL; CAPRYLYL GLYCOL; BIXA ORELLANA SEED; .ALPHA.-TOCOPHEROL; GREEN TEA LEAF; CUCUMBER; HYALURONIC ACID

SUPPORT SERUM FORTIFIED

DRUG FACTS

ACTIVE INGREDIENT

4% COLLOIDAL SULFUR

PURPOSE

ACNE TREATMENT CREAM.

USES

HELPS CLEAR UP ACNE PIMPLES, WHITEHEADS AND BLACKHEADS AND ALLOWS SKIN TO HEAL. HELPS PREVENT NEW ACNE BLEMISHES FROM FORMING. PENETRATES PORES TO CONTROL ACNE PIMPLES, BLACKHEADS AND WHITEHEADS.

WARNINGS

FOR EXTERNAL USE ONLY. DO NOT USE ON - BROKEN SKIN - LARGE AREAS OF THE SKIN.

WHEN USING THIS PRODUCT - APPLY ONLY TO AREAS WITH ACNE. WHEN USING THIS PRODUCT - SKIN IRRITATION AND DRYNESS IS MORE LIKELY TO OCCUR IF YOU USE ANOTHER TOPICAL ACNE MEDICATION AT THE SAME TIME. IF IRRITATION OCCURS, ONLY USE ONE TOPICAL ACNE MEDICATION AT A TIME.

KEEP OUT OF REACH OF CHILDREN

DIRECTIONS

- CLEANSE THE SKIN THOROUGHLY BEFORE APPLYING THIS PRODUCT - COVER THE ENTIRE AFFECTED AREA ONCE DAILY - BECAUSE EXCESSIVE DRYING OF THE SKIN MAY OCCUR, START WITH ONE APPLICATION DAILY AS DIRECTED BY A DOCTOR. CAN BE INCREASED TO UP TO 3 TIMES PER DAY - IF BOTHERSOME DRYNESS OR PEELING OCCURS, REDUCE APPLICATION EVERY OTHER DAY. FOLLOW WITH DESIRED MOISTURIZER. SENSITIVITY TEST FOR A NEW USER: APPLY PRODUCT SPARINGLY TO ONE OR TWO SMALL, AFFECTED AREAS DURING THE FIRST 3 DAYS. IF NO DISCOMFORT OCCURS, FOLLOW THE DIRECTIONS STATED.

INACTIVE INGREDIENTS

WATER, CAPRYLIC/CAPRIC TRIGLYCERIDE, DICAPRYLYL CARBONATE, GLYCERYL STEARATE, CETYL ALCOHOL, HYDROXYETHYL ACRYLATE/SODIUM ACRYLOYLDIMETHYL TAURATE COPOLYMER, SQUALANE, POLYSORBATE 60, AVOCADO SEED OIL, GLYCERIN, PENTAPEPTIDE-59. HYDROGENATED LECITHIN, SHEA BUTTER [DENOTES CERTIFIED ORGANIC INGREDIENT] , PHENETHYL ALCOHOL, ETHYLHEXYLGLYCERIN, MALTODEXTRIN, STEARIC ACID, GLYCERYL STEARATE CITRATE, STEARYL ALCOHOL, 1,2-HEXANEDIOL, CAPRYLYL GLYCOL, BIXA ORELLANA SEED EXTRACT, VITAMIN E, MEADOWSWEET FLOWER EXTRACT, GREEN TEA LEAF EXTRACT, CUCUMBER EXTRACT, & HYALURONIC ACID.

QUESTIONS OR COMMENTS?

CALL: 1-888-749-4998
VISIT: ZENMED.COM
EMAIL: INFO@ZENMED.COM

PRINCIPAL DISPLAY PANEL - 60 ML Bottle Label

SUPPORT
SERUM
FORTIFIED

Extra Strength,
Medicated
Formula

With Natural
Extracts to Clear
Troubled Skin

VEGAN,
PLANT-BASED

CRUELTY-FREE
CERTIFIED

60 ML | 2 fl OZ

ZENMED®
Reconstructive Skincare